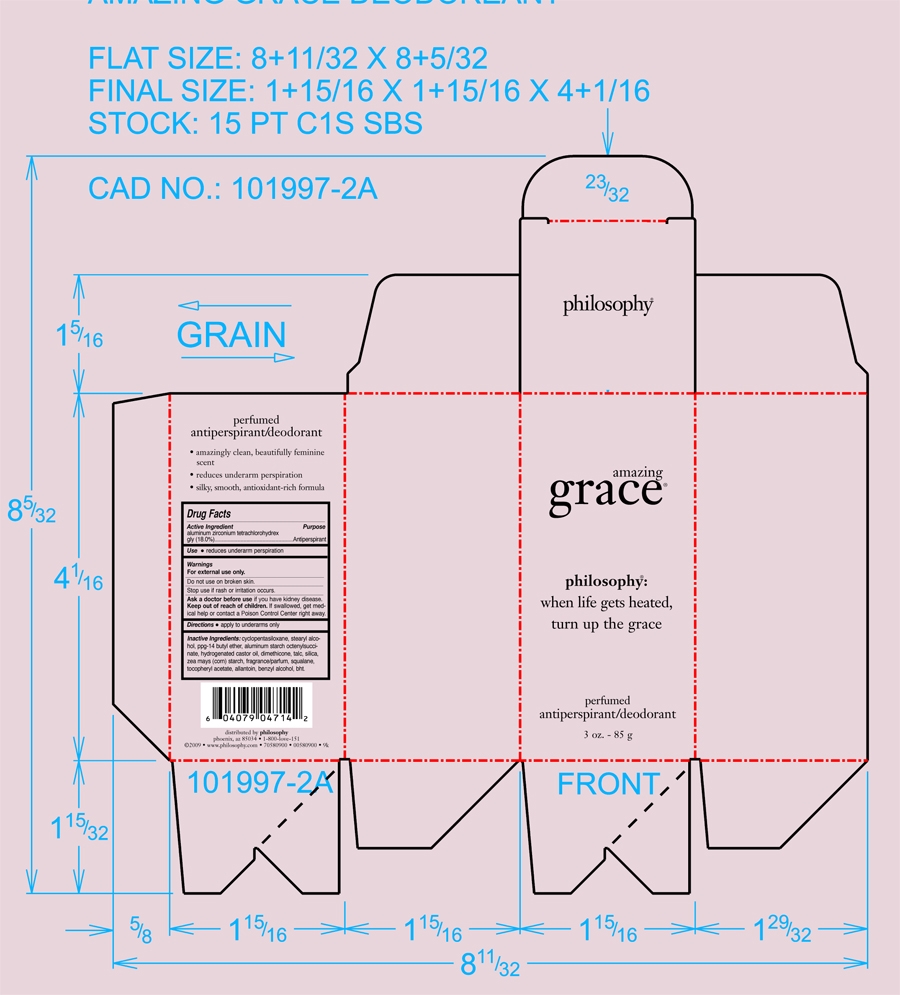 DRUG LABEL: Amazing Grace Antiperspirant and Deodorant
NDC: 53135-825 | Form: STICK
Manufacturer: Raani Corporation
Category: otc | Type: HUMAN OTC DRUG LABEL
Date: 20100223

ACTIVE INGREDIENTS: Aluminum Zirconium Tetrachlorohydrex Gly 180 mg/1 g
INACTIVE INGREDIENTS: Cyclomethicone 5; Stearyl Alcohol; Hydrogenated Castor Oil; Dimethicone; Talc; Silicon Dioxide; Starch, Corn; Squalane; .alpha.-tocopherol acetate, d-; Allantoin; Benzyl Alcohol; Butylated Hydroxytoluene

Drug Facts

Active Ingredient...........

Aluminum Zirconium Tetrachlorhydrex-Gly........18.0%

PURPOSE

Use: Reduces underarm perspiration.

Ask doctor before use if you have kidney disease.

Keep out of reach of children. if swallowed get medical help or contact a Poison Control Center right away.

INACTIVE INGREDIENT

cyclopentasiloxane, stearyl alchol, ppg-14 butyl ether, aluminum starch octenyl succinate, hydrogenated castor oil, dimethicone, talc, silica, corn starch, fragrance, squalane, tocopheryl acetate, allantoin, benzyl alcohol, bht.

Do not use on broken skin.

Stop use if rash or irritation occurs.